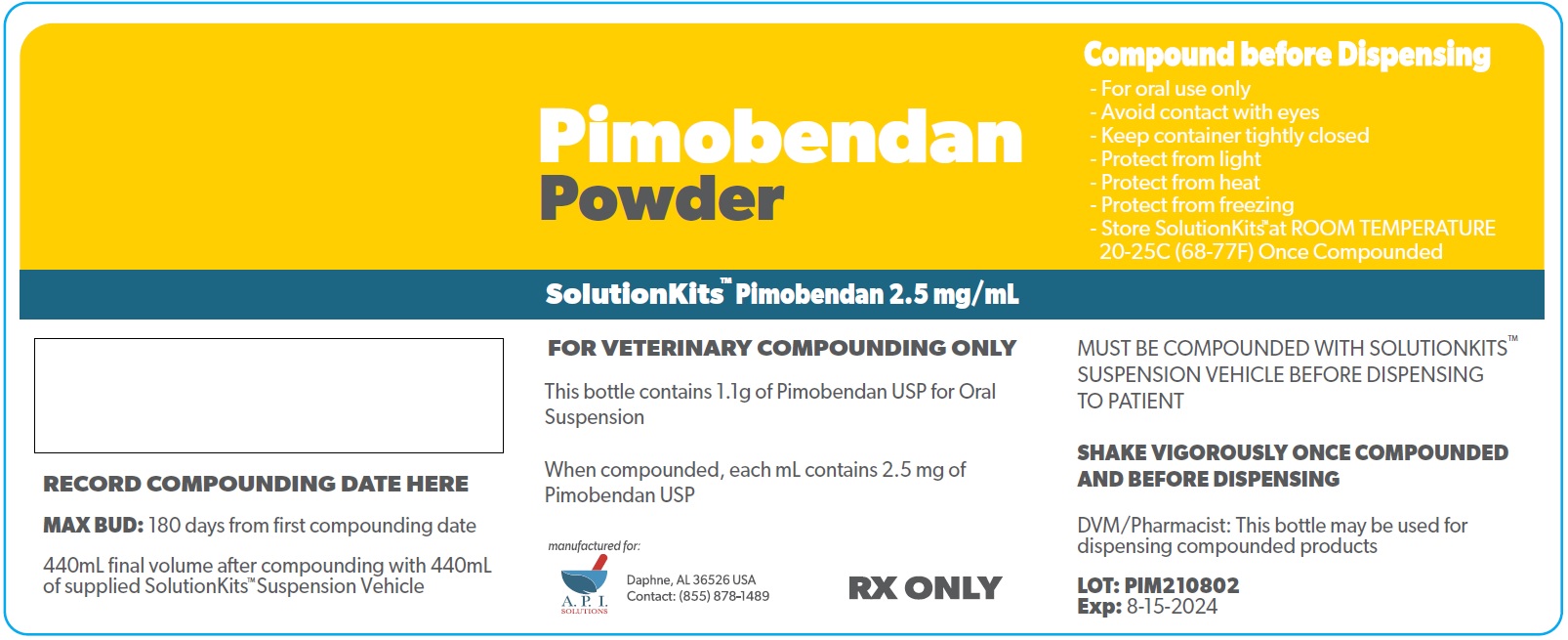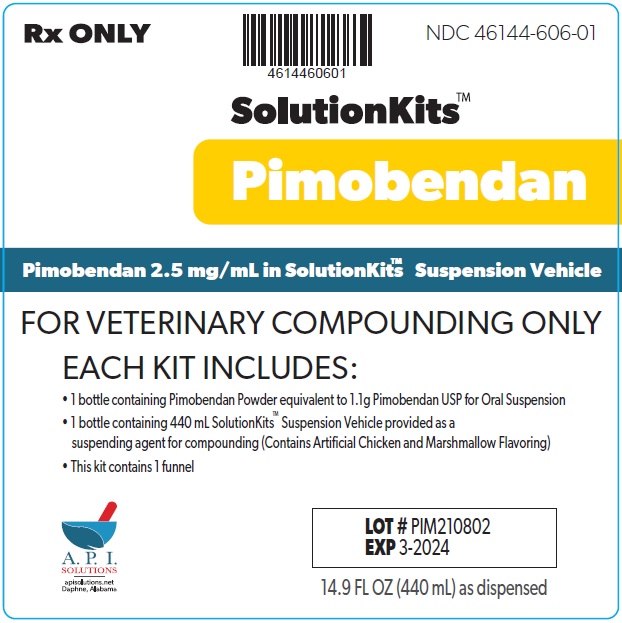 DRUG LABEL: SolutitionKits
NDC: 46144-606 | Form: KIT | Route: NOT APPLICABLE
Manufacturer: API Solutions
Category: other | Type: BULK INGREDIENT - ANIMAL DRUG
Date: 20260122

ACTIVE INGREDIENTS: PIMOBENDAN 1 g/1 g
INACTIVE INGREDIENTS: MEDIUM-CHAIN TRIGLYCERIDES; COCONUT OIL; BUTYLATED HYDROXYANISOLE; POLYGLYCERYL-3 OLEATE; SILICON DIOXIDE; .ALPHA.-TOCOPHEROL

SolutionsKits Pimobendan

Rx ONLY

NDC 46144-606-01

SolutionKits™Pimobendan

Pimobendan 2.5 mg/mL in SolutionKits™ Suspension Vehicle

FOR VETERINARY COMPOUNDING ONLY

EACH KIT INCLUDES:

1 bottle containing Pimobendan Powder equivalent to 1.1g Pimobendan USP for Oral Suspension

1 bottle containing 440 mL SolutionKits™ Suspension Vehicle provided as a suspending agent for compounding (Contains Artificial Chicken and Marshmallow Flavoring)

This kit contains 1 funnel

A.P.I.

Solutions

Daphne, AL USA

14.9 FL OZ (440 mL) as dispensed